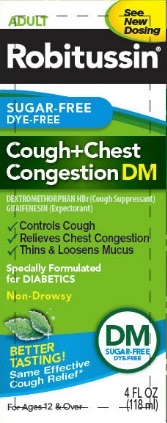 DRUG LABEL: Robitussin Sugar-Free Dye-Free Cough Plus Chest Congestion DM
NDC: 0031-8759 | Form: SOLUTION
Manufacturer: Haleon US Holdings LLC
Category: otc | Type: HUMAN OTC DRUG LABEL
Date: 20240315

ACTIVE INGREDIENTS: DEXTROMETHORPHAN HYDROBROMIDE 20 mg/20 mL; GUAIFENESIN 200 mg/20 mL
INACTIVE INGREDIENTS: ANHYDROUS CITRIC ACID; CARBOXYMETHYLCELLULOSE SODIUM, UNSPECIFIED; GLYCERIN; MENTHOL, UNSPECIFIED FORM; POLYETHYLENE GLYCOL, UNSPECIFIED; PROPYLENE GLYCOL; WATER; SODIUM BENZOATE; SODIUM CITRATE, UNSPECIFIED FORM; SODIUM GLUCONATE; SUCRALOSE; TRIACETIN; XANTHAN GUM

Drug Facts

ACTIVE INGREDIENT

PURPOSE

Active ingredients (in each 20 ml) | Purposes
Dextromethorphan HBr, USP 20 mg | Cough suppressant
Guaifenesin, USP 200 mg | Expectorant

Uses

- temporarily relieves cough due to minor throat and bronchial irritation as may occur with a cold
- helps loosen phlegm (mucus) and thin bronchial secretions to drain bronchial tubes

Warnings

Do not use if you are now taking a prescription monoamine oxidase inhibitor (MAOI) (certain drugs for depression, psychiatric, or emotional conditions, or Parkinson's disease), or for 2 weeks after stopping the MAOI drug. If you do not know if your prescription drug contains an MAOI, ask a doctor or pharmacist before taking this product.

Ask a doctor before use if you have

- cough that occurs with too much phlegm (mucus)
- cough that lasts or is chronic such as occurs with smoking, asthma, chronic bronchitis, or emphysema

Stop use and ask a doctor if cough lasts more than 7 days, comes back, or is accompanied by fever, rash, or persistent headache. These could be signs of a serious condition.

PREGNANCY OR BREAST FEEDING

If pregnant or breast-feeding, ask a health professional before use.

Keep out of reach of children. In case of overdose, get medical help or contact a Poison Control Center right away.

Directions

- do not take more than 6 doses in any 24-hour period
- measure only with dosing cup provided
- keep dosing cup with product
- ml = milliliter
- this adult product is not intended for use in children under 12 years of age

age | dose
adults and children 12 years and over | 20 ml every 4 hours
children under 12 years | do not use

Other information

- each 20 ml contains: sodium 20 mg
- store at 20-25°C (68-77°F). Do not refrigerate.

Inactive ingredients

anhydrous citric acid, carboxymethylcellulose sodium, glycerin, menthol, natural and artificial flavors, polyethylene glycol, propylene glycol, purified water, sodium benzoate, sodium citrate, sodium gluconate, sucralose, triacetin, xanthan gum

Questions or comments?

call weekdays from 9 AM to 5 PM EST at 1-800-762-4675

Distributed by:
Pfizer, Madison, NJ 07940 US

PRINCIPAL DISPLAY PANEL - 118 ml Bottle Carton

ADULT

See
New
Dosing

Robitussin®

SUGAR-FREE
DYE-FREE

Cough+Chest
Congestion DM

DEXTROMETHORPHAN HBr (Cough Suppressant)
GUAIFENESIN (Expectorant)

1. Controls Cough
2. Relieves Chest Congestion
3. Thins & Loosens Mucus

Specially Formulated
for DIABETICS

Non-Drowsy

DM
SUGAR-FREE
DYE-FREE

BETTER
TASTING!
Same Effective
Cough Relief*

For Ages 12 & Over

4 FL OZ
(118 ml)